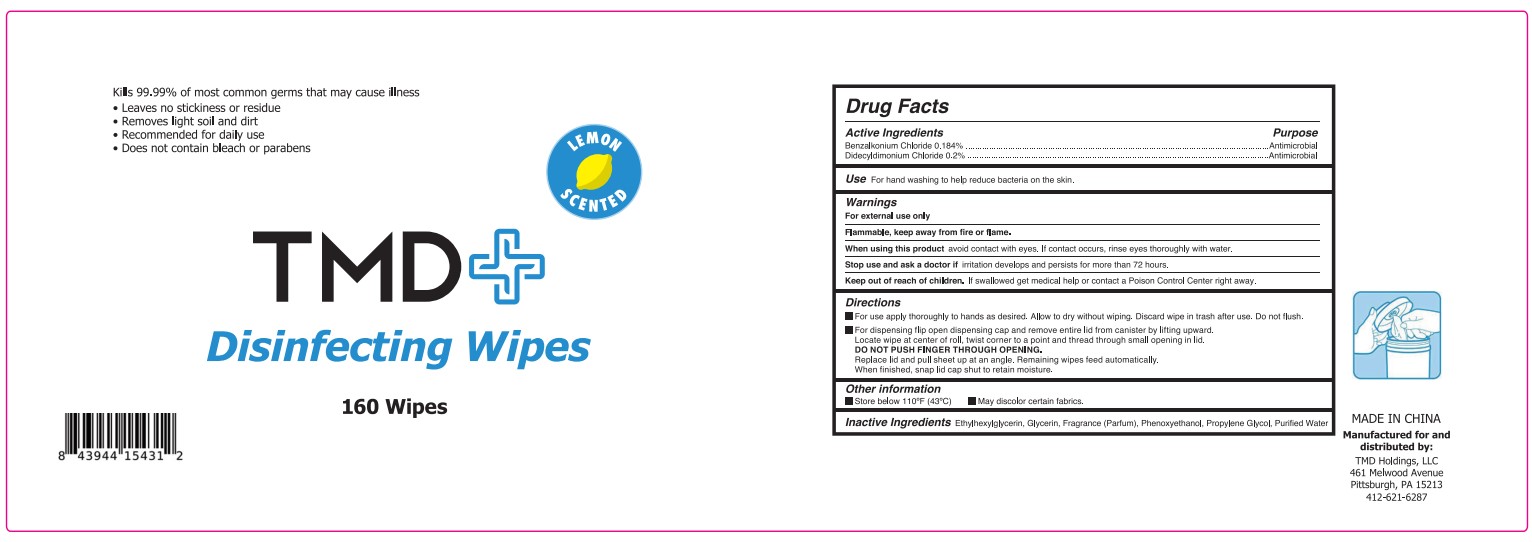 DRUG LABEL: DISINFECTING WIPES
NDC: 80297-031 | Form: CLOTH
Manufacturer: Tmd Holdings, Llc
Category: otc | Type: HUMAN OTC DRUG LABEL
Date: 20200826

ACTIVE INGREDIENTS: BENZALKONIUM CHLORIDE 0.184 g/100 g; DIDECYLDIMONIUM CHLORIDE 0.2 g/100 g
INACTIVE INGREDIENTS: GLYCERIN 0.1 g/100 g; PROPYLENE GLYCOL 0.1 g/100 g; WATER 98.786 g/100 g; PHENOXYETHANOL 0.5 g/100 g; ETHYLHEXYLGLYCERIN 0.1 g/100 g; FRAGRANCE LAVENDER & CHIA F-153480 0.03 g/100 g

Active Ingredient(s)

Benzalkonium Chloride 0.184% w/w, Purspose: Antimicrobial

Didecyldimonium Chloride 0.2% w/w, Purspose: Antimicrobial

Purpose

Antiseptic, Hand Sanitizer

Use

For hand washing to help reduce bacteria on the skin.

Warnings

For external use only. Flammable. Keep away from heat or flame

Do not use

- in children less than 2 months of age
- on open skin wounds

When using this product keep out of eyes, ears, and mouth. In case of contact with eyes, rinse eyes thoroughly with water.
Stop use and ask a doctor if irritation or rash occurs. These may be signs of a serious condition.
Keep out of reach of children. If swallowed, get medical help or contact a Poison Control Center right away.

Stop use and ask a doctor if irritation develops and persists for more than 72 hours.

Keep out of reach of children. If swallowed, get medical help or contact a Poison Control Center right away.

Directions

- For use apply thoroughly to hands as desired. Allow to dry without wiping. Discard wipe in trash after use. Do not flush.
- For dispensing flip open dispensing cap and remove entire lid from canister by lifting upward.
- Locate wipe at center of roll, twist corner to a point and thread through small opening in lid.
- DO NOT PUSH FINGER THROUGH OPENING.
- Replace lid and pull sheet up at an angle. Remaining wipes feed automatically.
- When finished, snap lid cap shut to retain moisture.

Other information

- Store below 110F(43C)
- May discolor certain fabrics.

Inactive ingredients

Ethylhexylglycerin, Glycerin, Fragrance(Parfum), Phenoxyethanol, Propylene Glycol, Purified water

Package Label - Principal Display Panel

160 Wipes NDC: 80297-031-01